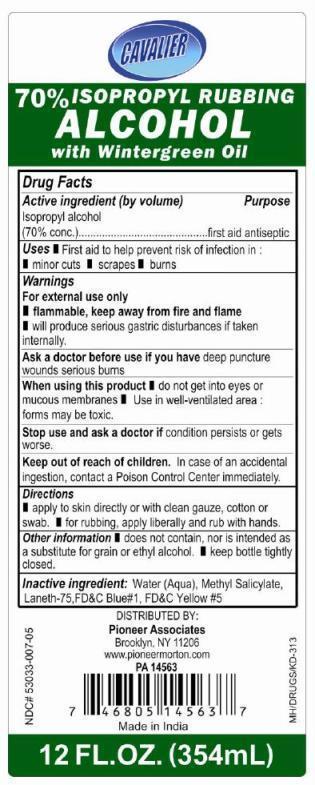 DRUG LABEL: ISOPROPYL RUBBING ALCOHOL WITH WINTERGREEN OIL
NDC: 53033-007 | Form: LIQUID
Manufacturer: Pioneer Associates
Category: otc | Type: HUMAN OTC DRUG LABEL
Date: 20130208

ACTIVE INGREDIENTS: ISOPROPYL ALCOHOL 70 mL/100 mL
INACTIVE INGREDIENTS: WATER; METHYL SALICYLATE; PEG-75 LANOLIN; FD&C BLUE NO. 1; FD&C YELLOW NO. 5

CAVALIER ISOPROPYL RUBBING ALCOHOL 70% WITH WINTERGREEN OIL

Active ingredient (by volume)

Isopropyl alcohol (70% conc.)

Purpose

first aid antiseptic

Uses

- First aid to help prevent risk of infection in:
- minor cuts
- scrapes
- burns

Warnings

For external use only

- flammable, keep away from fire and flame
- will produce serious gastric disturbances if taken internally.

Ask a doctor before use if you have deep puncture wounds or serious burns

When using this product

- do not get into eyes or mucous membranes
- use in well-ventilated area: forms may be toxic

Stop use and ask a doctor if condition persists or gets worse

Keep out of reach of children.

In case of an accidental ingestion, contact a Poison Control Center immediately

Directions

- apply to skin directly or with clean gauze, cotton or swab
- for rubbing apply, liberally and rub with hands

Other information

- does not contain, nor is intended as a substitute for grain or ethyl alcohol
- keep bottle tightly closed

Inactive ingredient

Water (Aqua), methyl salicylate, laneth-75, FD&C Blue #1, FD&C Yellow #5

PRINCIPAL DISPLAY PANEL

CAVALIER ISOPROPYL RUBBING ALCOHOL 70% WITH WINTERGREEN OIL

FIRST AID ANTISEPTIC

12 FL.OZ (354 mL)